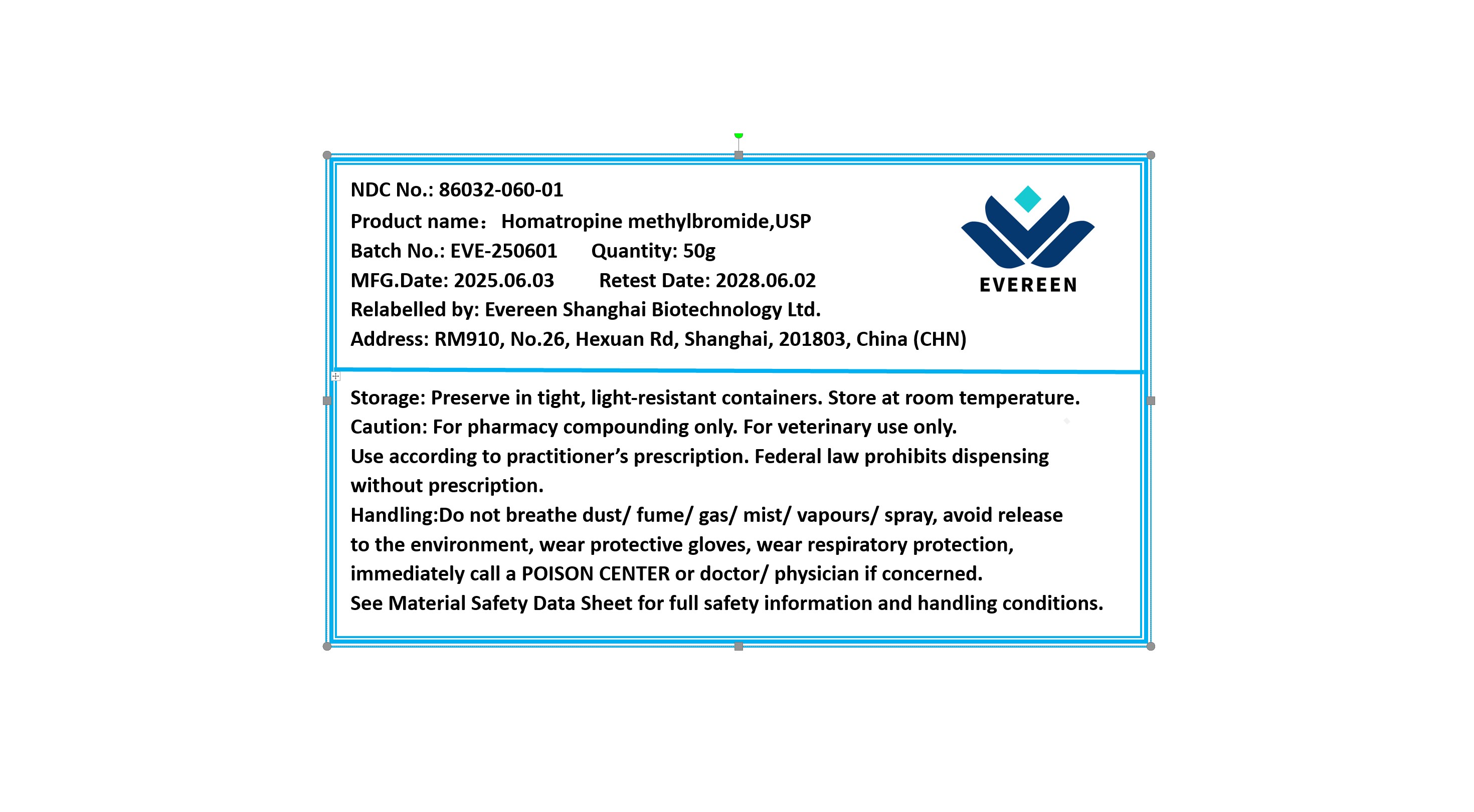 DRUG LABEL: Homatropine Methylbromide
NDC: 86032-060 | Form: POWDER
Manufacturer: Evereen Shanghai Biotechnology Ltd.
Category: other | Type: BULK INGREDIENT - ANIMAL DRUG
Date: 20250919

ACTIVE INGREDIENTS: HOMATROPINE METHYLBROMIDE 1 g/1 g

Homatropine Methylbromide